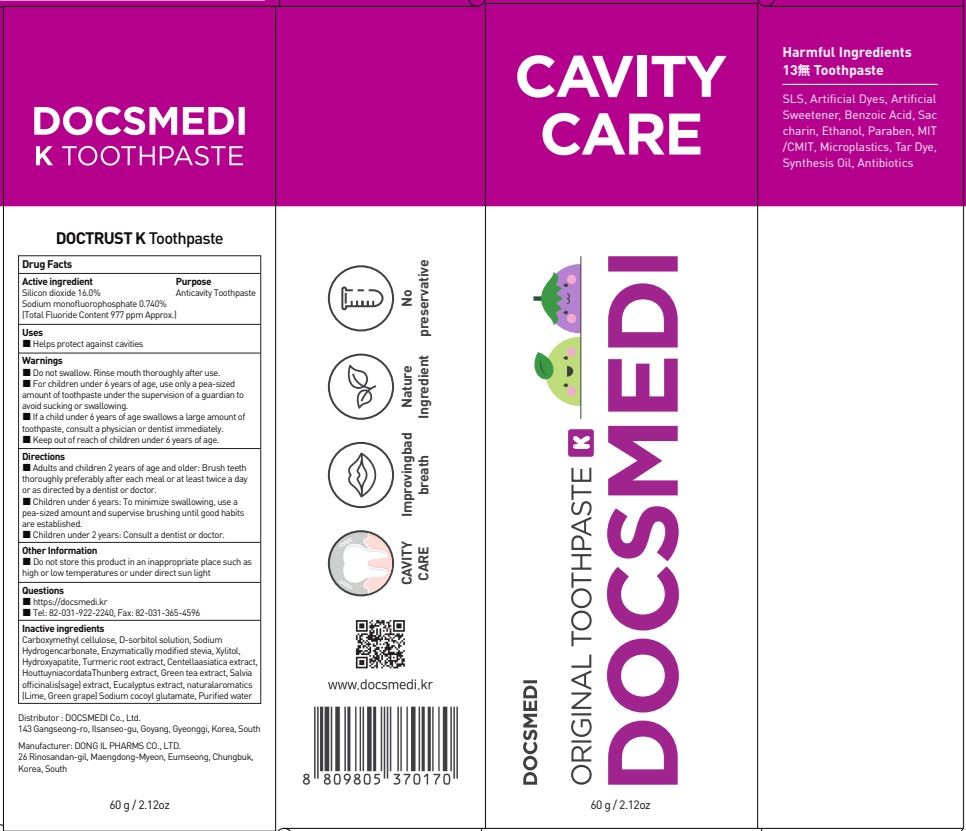 DRUG LABEL: DOCTRUST K Tooth
NDC: 73242-1123 | Form: GEL, DENTIFRICE
Manufacturer: DONG IL PHARMS CO.,LTD
Category: otc | Type: HUMAN OTC DRUG LABEL
Date: 20251125

ACTIVE INGREDIENTS: SILICON DIOXIDE 16 g/100 g; SODIUM MONOFLUOROPHOSPHATE 0.74 g/100 g
INACTIVE INGREDIENTS: CARBOXYMETHYLCELLULOSE; SORBITOL

ACTIVE INGREDIENT

Silicon dioxide 16.0%
Sodium monofluorophosphate 0.740%
(Total Fluoride Content 977 ppm Approx.)

Inactive ingredients

Carboxymethyl cellulose, D-sorbitol solution, Sodium Hydrogencarbonate, Enzymatically modified stevia, Xylitol, Hydroxyapatite, Turmeric root extract, Centellaasiatica extract, HouttuyniacordataThunberg extract, Green tea extract, Salvia officinalis(sage) extract, Eucalyptus extract, naturalaromatics(Lime, Green grape) Sodium cocoyl glutamate, Purified water

PURPOSE

Anticavity Toothpaste

WARNINGS

■ Do not swallow. Rinse mouth thoroughly after use.

■ For children under 6 years of age, use only a pea-sized amount of toothpaste under the supervision of a guardian to avoid sucking or swallowing.

■ If a child under 6 years of age swallows a large amount of toothpaste, consult a physician or dentist immediately.

■ Keep out of reach of children under 6 years of age.

KEEP OUT OF REACH OF CHILDREN

■ Keep out of the reach of children under 6 years of age.

Uses

■ Helps protect against cavities

Directions

■ Adults and children 2 years of age and older: Brush teeth thoroughly preferably after each meal or at least twice a day or as directed by a dentist or doctor.
■ Children under 6 years: To minimize swallowing, use a pea-sized amount and supervise brushing until good habits are established.
■ Children under 2 years: Consult a dentist or doctor.

Other Information

■ Do not store this product in an inappropriate place such as high or low temperatures or under direct sun light

Questions

■ https://docsmedi.kr

■ Tel: 82-031-922-2240, Fax: 82-031-365-4596